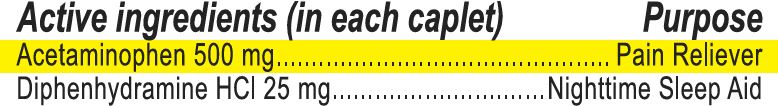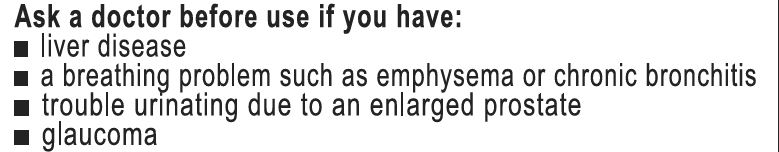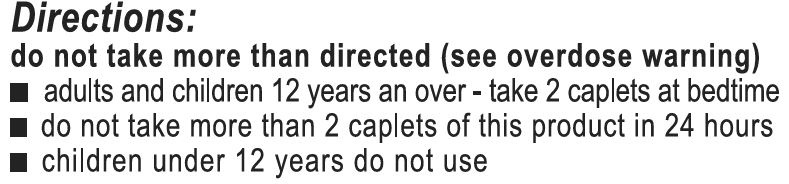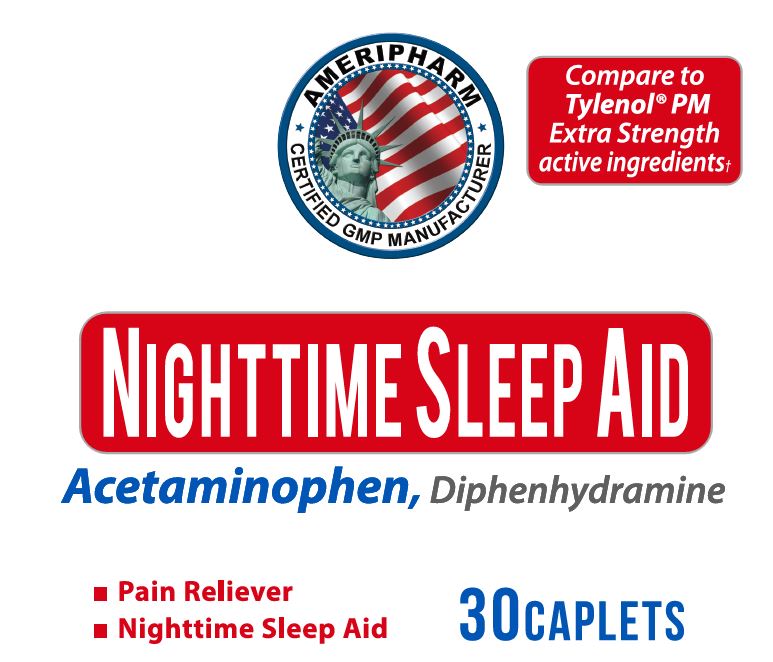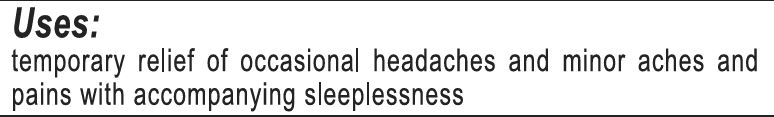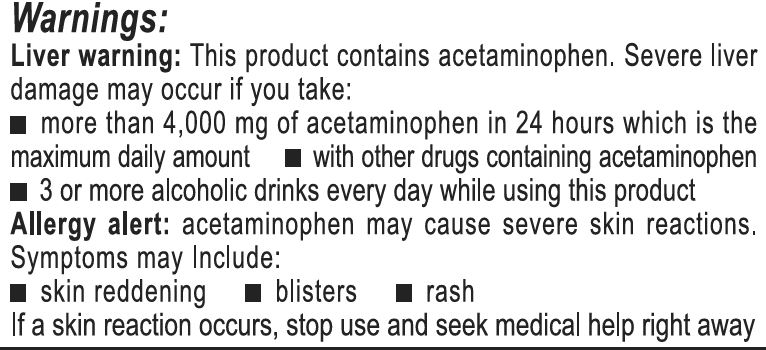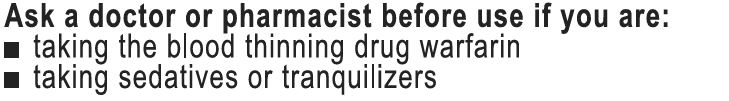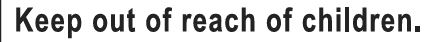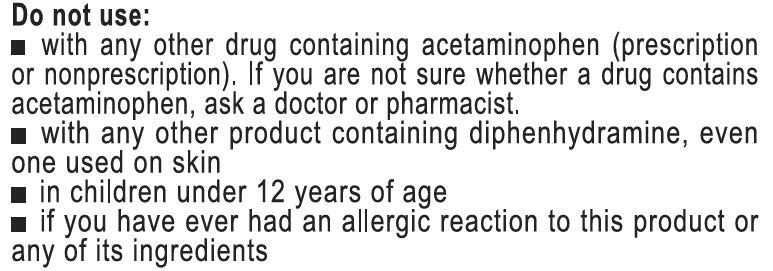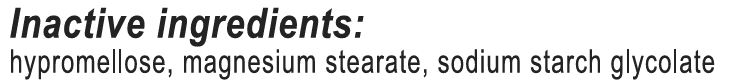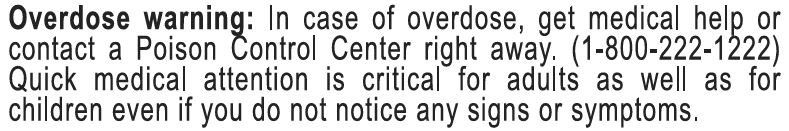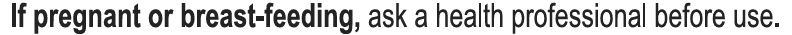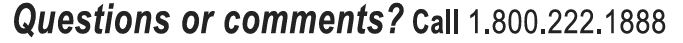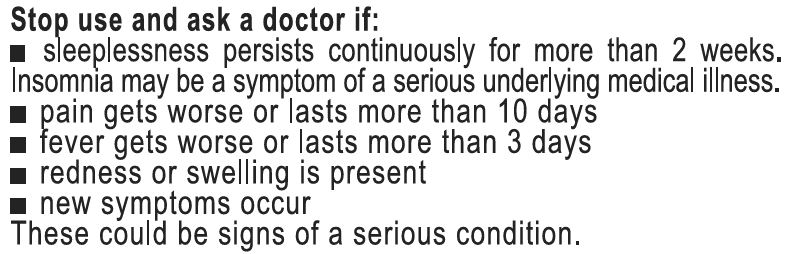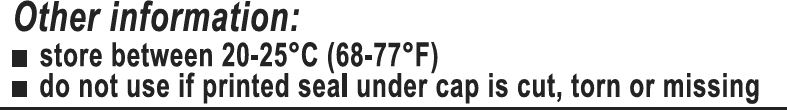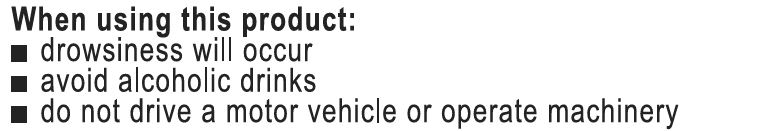 DRUG LABEL: Nighttime Sleep Aid
NDC: 69732-005 | Form: TABLET
Manufacturer: Hi-Tech Nutraceuticals, LLC
Category: otc | Type: HUMAN OTC DRUG LABEL
Date: 20221231

ACTIVE INGREDIENTS: DIPHENHYDRAMINE HYDROCHLORIDE 25 mg/1 1; ACETAMINOPHEN 500 mg/1 1
INACTIVE INGREDIENTS: SODIUM STARCH GLYCOLATE TYPE A; HYPROMELLOSE, UNSPECIFIED; MAGNESIUM STEARATE

Sleep Aid